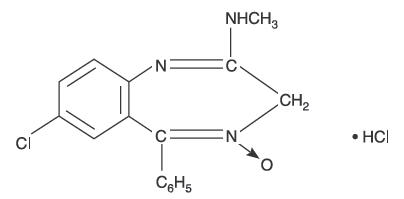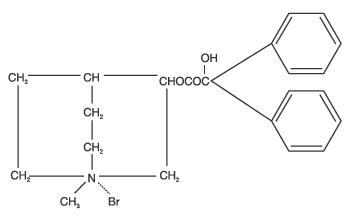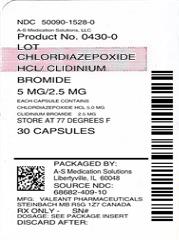 DRUG LABEL: Chlordiazepoxide Hydrochloride and Clidinium Bromide
NDC: 50090-1528 | Form: CAPSULE
Manufacturer: A-S Medication Solutions
Category: prescription | Type: HUMAN PRESCRIPTION DRUG LABEL
Date: 20171122

ACTIVE INGREDIENTS: CHLORDIAZEPOXIDE HYDROCHLORIDE 5 mg/1 1; CLIDINIUM BROMIDE 2.5 mg/1 1
INACTIVE INGREDIENTS: starch, corn; LACTOSE, UNSPECIFIED FORM; talc; methylparaben; propylparaben; potassium sorbate; D&C yellow No. 10; FD&C blue No. 1; FD&C green No. 3

Chlordiazepoxide HCl/
Clidinium Bromide
CAPSULES

to control emotional
and somatic factors
in gastrointestinal disorders

DESCRIPTION

Chlordiazepoxide HCl/Clidinium Bromide combines in a single capsule formulation the antianxiety action of chlordiazepoxide hydrochloride and the anticholinergic/spasmolytic effects of clidinium bromide, both exclusive developments of Roche research.

Each Chlordiazepoxide HCl/Clidinium Bromide capsule contains 5 mg chlordiazepoxide hydrochloride and 2.5 mg clidinium bromide. Each capsule also contains corn starch, lactose and talc. Gelatin capsule shells may contain methyl and propyl parabens and potassium sorbate, with the following dye systems: D&C Yellow No. 10 and either FD&C Blue No. 1 or FD&C Green No. 3.

Chlordiazepoxide hydrochloride is a versatile, therapeutic agent of proven value for the relief of anxiety and tension. It is indicated when anxiety, tension or apprehension are significant components of the clinical profile. It is among the safer of the effective psychopharmacologic compounds.

Chlordiazepoxide hydrochloride is 7-chloro-2-methylamino-5-phenyl-3H-1,4-benzodiazepine 4-oxide hydrochloride. A colorless, crystalline substance, it is soluble in water. It is unstable in solution and the powder must be protected from light. The molecular weight is 336.22. The structural formula of chlordiazepoxide hydrochloride is as follows:

Clidinium bromide is a synthetic anticholinergic agent which has been shown in experimental and clinical studies to have a pronounced antispasmodic and antisecretory effect on the gastrointestinal tract. Structurally clidinium bromide is:

ANIMAL PHARMACOLOGY

Chlordiazepoxide hydrochloride has been studied extensively in many species of animals and these studies are suggestive of action on the limbic system of the brain, which recent evidence indicates is involved in emotional responses.

Hostile monkeys were made tame by oral drug doses which did not cause sedation. Chlordiazepoxide hydrochloride revealed a "taming" action with the elimination of fear and aggression. The taming effect of chlordiazepoxide hydrochloride was further demonstrated in rats made vicious by lesions in the septal area of the brain. The drug dosage which effectively blocked the vicious reaction was well below the dose which caused sedation in these animals.

The oral LD50 of single doses of chlordiazepoxide hydrochloride, calculated according to the method of Miller and Tainter, is 720 ± 51 mg/kg as determined in mice observed over a period of 5 days following dosage.

Clidinium bromide is an effective anticholinergic agent with activity approximating that of atropine sulfate against acetylcholine-induced spasms in isolated intestinal strips. On oral administration in mice it proved an effective antisialagogue in preventing pilocarpine-induced salivation. Spontaneous intestinal motility in both rats and dogs is reduced following oral dosing with 0.1 to 0.25 mg/kg. Potent cholinergic ganglionic blocking effects (vagal) are produced with intravenous usage in anesthetized dogs.

Oral doses of 2.5 mg/kg to dogs produced signs of nasal dryness and slight pupillary dilation. In two other species, monkeys and rabbits, doses of 5 mg/kg, po, given three times daily for 5 days did not produce apparent secretory or visual changes.

The oral LD50 of single doses of clidinium bromide is 860 ± 57 mg/kg as determined in mice observed over a period of 5 days following dosage; the calculations were made according to the method of Miller and Tainter.

Effects on Reproduction

Reproduction studies in rats fed chlordiazepoxide hydrochloride, 10, 20 and 80 mg/kg daily, and bred through one or two matings showed no congenital anomalies, nor were there adverse effects on lactation of the dams or growth of the newborn. However, in another study at 100 mg/kg daily there was noted a significant decrease in the fertilization rate and a marked decrease in the viability and body weight of offspring which may be attributable to sedative activity, thus resulting in lack of interest in mating and lessened maternal nursing and care of the young. One neonate in each of the first and second matings in the rat reproduction study at the 100 mg/kg dose exhibited major skeletal defects. Further studies are in progress to determine the significance of these findings.

Two series of reproduction experiments with clidinium bromide were carried out in rats, employing dosages of 2.5 and 10 mg/kg daily in each experiment. In the first experiment clidinium bromide was administered for a 9-week interval prior to mating; no untoward effect on fertilization or gestation was noted. The offspring were taken by caesarean section and did not show a significant incidence of congenital anomalies when compared to control animals. In the second experiment adult animals were given clidinium bromide for 10 days prior to and through two mating cycles. No significant effects were observed on fertility, gestation, viability of offspring or lactation, as compared to control animals, nor was there a significant incidence of congenital anomalies in the offspring derived from these experiments.

A reproduction study of Chlordiazepoxide HCl/Clidinium Bromide was carried out in rats through two successive matings. Oral daily doses were administered in two concentrations: 2.5 mg/kg chlordiazepoxide hydrochloride with 1.25 mg/kg clidinium bromide or 25 mg/kg chlordiazepoxide hydrochloride with 12.5 mg/kg clidinium bromide. In the first mating no significant differences were noted between the control or the treated groups, with the exception of a slight decrease in the number of animals surviving during lactation among those receiving the highest dosage. As with all anticholinergic drugs, an inhibiting effect on lactation may occur. In the second mating similar results were obtained except for a slight decrease in the number of pregnant females and in the percentage of offspring surviving until weaning. No congenital anomalies were observed in both matings in either the control or treated groups. Additional animal reproduction studies are in progress.

INDICATIONS AND USAGE

Based on a review of this drug by the National Academy of Sciences — National Research Council and/or other information, FDA has classified the indications as follows:

"Possibly" effective: as adjunctive therapy in the treatment of peptic ulcer and in the treatment of the irritable bowel syndrome (irritable colon, spastic colon, mucous colitis) and acute enterocolitis.

Final classification of the less-than-effective indications requires further investigation.

CONTRAINDICATIONS

Chlordiazepoxide HCl/Clidinium Bromide is contraindicated in the presence of glaucoma (since the anticholinergic component may produce some degree of mydriasis) and in patients with prostatic hypertrophy and benign bladder neck obstruction. It is contraindicated in patients with known hypersensitivity to chlordiazepoxide hydrochloride and/or clidinium bromide.

WARNINGS

As in the case of other preparations containing CNS-acting drugs, patients receiving Chlordiazepoxide HCl/Clidinium Bromide should be cautioned about possible combined effects with alcohol and other CNS depressants. For the same reason, they should be cautioned against hazardous occupations requiring complete mental alertness such as operating machinery or driving a motor vehicle.

Usage in Pregnancy

An increased risk of congenital malformations associated with the use of minor tranquilizers (chlordiazepoxide, diazepam and meprobamate) during the first trimester of pregnancy has been suggested in several studies. Because use of these drugs is rarely a matter of urgency, their use during this period should almost always be avoided. The possibility that a woman of childbearing potential may be pregnant at the time of institution of therapy should be considered. Patients should be advised that if they become pregnant during therapy or intend to become pregnant they should communicate with their physicians about the desirability of discontinuing the drug.

As with all anticholinergic drugs, an inhibiting effect on lactation may occur (see Animal Pharmacology).

OVERDOSAGE

Manifestations of chlordiazepoxide hydrochloride overdosage include somnolence, confusion, coma and diminished reflexes. Respiration, pulse and blood pressure should be monitored, as in all cases of drug overdosage, although, in general, these effects have been minimal following chlordiazepoxide hydrochloride overdosage.

While the signs and symptoms of Chlordiazepoxide HCl/Clidinium Bromide overdosage may be produced by either of its components, usually such symptoms will be overshadowed by the anticholinergic actions of clidinium bromide. The symptoms of overdosage of clidinium bromide are excessive dryness of mouth, blurring of vision, urinary hesitancy and constipation.

General supportive measures should be employed, along with immediate gastric lavage. Administer physostigmine 0.5 to 2 mg at a rate of no more than 1 mg per minute. This may be repeated in 1 to 4 mg doses if arrhythmias, convulsions or deep coma recur. Intravenous fluids should be administered and an adequate airway maintained. Hypotension may be combated by the use of levarterenol or metaraminol. Methylphenidate or caffeine and sodium benzoate may be given to combat CNS-depressive effects. Dialysis is of limited value. Should excitation occur, barbiturates should not be used. As with the management of intentional overdosage with any drug, it should be borne in mind that multiple agents may have been ingested.

Withdrawal symptoms of the barbiturate type have occurred after the discontinuation of benzodiazepines (see DRUG ABUSE AND DEPENDENCE section).

PRECAUTIONS

In debilitated patients, it is recommended that the dosage be limited to the smallest effective amount to preclude the development of ataxia, oversedation or confusion (not more than 2 Chlordiazepoxide HCl/Clidinium Bromide capsules per day initially, to be increased gradually as needed and tolerated). In general, the concomitant administration of Chlordiazepoxide HCl/Clidinium Bromide and other psychotropic agents is not recommended. If such combination therapy seems indicated, careful consideration should be given to the pharmacology of the agents to be employed — particularly when the known potentiating compounds such as the MAO inhibitors and phenothiazines are to be used. The usual precautions in treating patients with impaired renal or hepatic function should be observed.

Paradoxical reactions to chlordiazepoxide hydrochloride, eg, excitement, stimulation and acute rage, have been reported in psychiatric patients and should be watched for during Chlordiazepoxide HCl/Clidinium Bromide therapy. The usual precautions are indicated when chlordiazepoxide hydrochloride is used in the treatment of anxiety states where there is any evidence of impending depression; it should be borne in mind that suicidal tendencies may be present and protective measures may be necessary. Although clinical studies have not established a cause and effect relationship, physicians should be aware that variable effects on blood coagulation have been reported very rarely in patients receiving oral anticoagulants and chlordiazepoxide hydrochloride.

Information for Patients

To assure the safe and effective use of benzodiazepines, patients should be informed that, since benzodiazepines may produce psychological and physical dependence, it is advisable that they consult with their physician before either increasing the dose or abruptly discontinuing this drug.

Pediatric Use

Safety and effectiveness in pediatric patients have not been established.

Geriatric Use

Geriatric subjects may be particularly prone to experiencing drowsiness, ataxia and confusion while receiving Chlordiazepoxide HCl/Clidinium Bromide. These effects can usually be avoided with proper dosage adjustment, although they have occasionally been observed even at the lower dosage ranges. Dosing in geriatric subjects should be initiated cautiously (no more than 2 capsules per day) and increased gradually if needed and tolerated (see DOSAGE AND ADMINISTRATION). Chlordiazepoxide HCl/Clidinium Bromide is contraindicated in the presence of glaucoma, prostatic hypertrophy and benign bladder neck obstruction (see CONTRAINDICATIONS).

ADVERSE REACTIONS

No side effects or manifestations not seen with either compound alone have been reported with the administration of Chlordiazepoxide HCl/Clidinium Bromide. However, the possibility of untoward effects which may be seen with either of these two compounds cannot be excluded.

When chlordiazepoxide hydrochloride has been used alone the necessity of discontinuing therapy because of undesirable effects has been rare. Drowsiness, ataxia and confusion have been reported in some patients — particularly the elderly and debilitated. While these effects can be avoided in almost all instances by proper dosage adjustment, they have occasionally been observed at the lower dosage ranges. In a few instances syncope has been reported.

Other adverse reactions reported during therapy with chlordiazepoxide hydrochloride include isolated instances of skin eruptions, edema, minor menstrual irregularities, nausea and constipation, extrapyramidal symptoms, as well as increased and decreased libido. Such side effects have been infrequent and are generally controlled with reduction of dosage. Changes in EEG patterns (low-voltage fast activity) have been observed in patients during and after chlordiazepoxide hydrochloride treatment.

Blood dyscrasias, including agranulocytosis, jaundice and hepatic dysfunction have occasionally been reported during therapy with chlordiazepoxide hydrochloride. When chlordiazepoxide hydrochloride treatment is protracted, periodic blood counts and liver function tests are advisable.

Adverse effects reported with use of Chlordiazepoxide HCl/Clidinium Bromide are those typical of anticolinergic agents, ie, dryness of the mouth, blurring of vision, urinary hesitancy and constipation. Constipation has occurred most often when Chlordiazepoxide HCl/Clidinium Bromide therapy has been combined with other spasmolytic agents and/or a low residue diet.

DRUG ABUSE AND DEPENDENCE

Withdrawal symptoms, similar in character to those noted with barbiturates and alcohol (convulsions, tremor, abdominal and muscle cramps, vomiting and sweating), have occurred following abrupt discontinuance of chlordiazepoxide. The more severe withdrawal symptoms have usually been limited to those patients who had received excessive doses over an extended period of time. Generally milder withdrawal symptoms (eg, dysphoria and insomnia) have been reported following abrupt discontinuance of benzodiazepines taken continuously at therapeutic levels for several months. Consequently, after extended therapy, abrupt discontinuation should generally be avoided and a gradual dosage tapering schedule followed. Addiction-prone individuals (such as drug addicts or alcoholics) should be under careful surveillance when receiving chlordiazepoxide or other psychotropic agents because of the predisposition of such patients to habituation and dependence.

DOSAGE AND ADMINISTRATION

Because of the varied individual responses to tranquilizers and anticholinergics, the optimum dosage of Chlordiazepoxide HCl/Clidinium Bromide varies with the diagnosis and response of the individual patient. The dosage, therefore, should be individualized for maximum beneficial effects. The usual maintenance dose is 1 or 2 capsules, 3 or 4 times a day administered before meals and at bedtime.

Geriatric Dosing

Dosage should be limited to the smallest effective amount to preclude the development of ataxia, oversedation or confusion. The initial dose should not exceed 2 Chlordiazepoxide HCl/Clidinium Bromide capsules per day, to be increased gradually as needed and tolerated.

HOW SUPPLIED

Product: 50090-1528

NDC: 50090-1528-0 30 CAPSULE in a BOTTLE

Manufactured in Canada by:
Valeant Pharmaceuticals International, Inc.
Steinbach, MB R5G 1Z7
Canada

Manufactured for:
Oceanside Pharmaceuticals
a division of Valeant Pharmaceuticals North America LLC
Bridgewater, NJ 08807 USA

LB0093-00
Rev. 03/13

Medication Guide

LIBRAX (lee braks)

(chlordiazepoxide HCl and clidinium bromide) capsules

What is the most important information I should know about Librax?

- Do not stop taking Librax without first talking to your healthcare provider. Stopping Librax suddenly can cause serious side effects.
- Taking Librax with opioid medicines, alcohol, or other central nervous system depressants (including street drugs) can cause severe drowsiness, breathing problems (respiratory depression), coma and death.
- Do not drive, operate heavy machinery, or do other dangerous activities until you know how Librax affects you.
- Do not drink alcohol or take other drugs that may make you sleepy or dizzy while taking Librax without first talking to your healthcare provider. When taken with alcohol or drugs that cause sleepiness or dizziness, Librax may make your sleepiness or dizziness much worse.
- Librax can cause abuse and dependence.
- Do not stop taking Librax all of a sudden. Stopping Librax suddenly can cause seizures, shaking, stomach and muscle cramps, vomiting and sweating.
- Physical dependence is not the same as drug addiction. Your healthcare provider can tell you more about the differences between physical dependence and drug addiction.

What is Librax?

- Librax is a prescription medicine that is used with other therapies for the treatment of:
- stomach (peptic) ulcers
- irritable bowel syndrome (IBS)
- inflammation of the colon called acute enterocolitis
- Librax contains the medicines chlordiazepoxide HCl and clidinium bromide.
- Librax can be abused or lead to dependence. Keep Librax in a safe place to prevent misuse and abuse. Selling or giving away Librax may harm others. Tell your healthcare provider if you have abused or been dependent on alcohol, prescription medicines or street drugs.
- It is not known if Librax is safe and effective in children.

Do not take Librax if you:

- have glaucoma
- have an enlarged prostate
- have a blockage of your bladder that causes problems with urination
- are allergic to chlordiazepoxide hydrochloride or clidinium bromide

Before you take Librax, tell your healthcare provider about all of your medical conditions, including if you:

- have eye problems
- have problems urinating or emptying your bladder
- have coordination problems
- have kidney or liver problems
- have a history of depression, mental illness, or suicidal thoughts
- have a history of drug or alcohol abuse or addiction
- have bleeding problems
- are pregnant or plan to become pregnant. Librax may harm your unborn baby. Avoid taking Librax during the first trimester of pregnancy. Tell your healthcare provider right away if you become pregnant during treatment with Librax.
- are breastfeeding or plan to breastfeed. Librax may pass through your breast milk and may harm your baby. Talk to your healthcare provider about the best way to feed your baby if you take Librax. Librax may decrease the amount of breast milk your body makes.

Tell your healthcare provider about all the medicines you take, including prescription and over-the-counter medicines, vitamins, and herbal supplements.

Taking Librax with certain other medicines can cause side effects or affect how well Librax or the other medicines work.

Do not start or stop other medicines without talking to your healthcare provider.

Especially tell your healthcare provider if you:

- take a monoamine oxidase inhibitor (MAOI) medicine or an anti-psychotic medicine called phenothiazine.

How should I take Librax?

- Take Librax exactly as your healthcare provider tells you to take it.
- Your healthcare provider may change your dose of Librax if needed. Do not change your dose of Librax or suddenly stop taking Librax without talking with your healthcare provider.
- If you take too much Librax, call your healthcare provider or go to the nearest hospital emergency room right away.

What are the possible side effects of Librax?

Librax may cause serious side effects, including: See “What is the most important information I should know about Librax?”

The most common side effects of Librax include:

- dry mouth
- blurred vision
- nausea
- constipation
- skin problems
- swelling
- irregular menstrual (periods) cycles
- increase and decreased desire for sex (libido)
- problems starting to urinate
- drowsiness, coordination problems, and confusion may happen, especially in people who are elderly or weak

These are not all the possible side effects of Librax.

Call your doctor for medical advice about side effects. You may report side effects to FDA at 1-800-FDA-1088.

How should I store Librax?

- Store Librax at room temperature 77°F (25°C).
- Keep Librax and all medicines out of the reach of children.

General information about the safe and effective use of Librax.

Medicines are sometimes prescribed for purposes other than those listed in a Medication Guide. Do not use Librax for a condition for which it was not prescribed. Do not give Librax to other people, even if they have the same symptoms that you have. It may harm them. You can ask your pharmacist or healthcare provider for information about Librax that is written for health professionals.

What are the ingredients in Librax?

Active ingredient: chlordiazepoxide hydrochloride and clidinium bromide

Inactive ingredients: corn starch, lactose and talc. Gelatin capsule shells may contain methyl and propyl parabens and potassium sorbate, with the following dye systems: D&C Yellow No. 10 and either FD&C Blue No.1 or FD&C Green No. 3.

Manufactured in Canada by: Valeant Pharmaceuticals International, Inc. Steinbach, MB R5G 1Z7 Canada

Manufactured for: Valeant Pharmaceuticals North America LLC Bridgewater, NJ 08807 USA

Librax is a trademark of Valeant Pharmaceuticals International, Inc. or its affiliates.

©Valeant Pharmaceuticals North America LLC

For more information, go to www.valeant.com or contact Valeant Pharmaceuticals North America LLC at 1-800-321-4576

This Medication Guide has been approved by the U.S. Food and Drug Administration

Issued: 01/2017